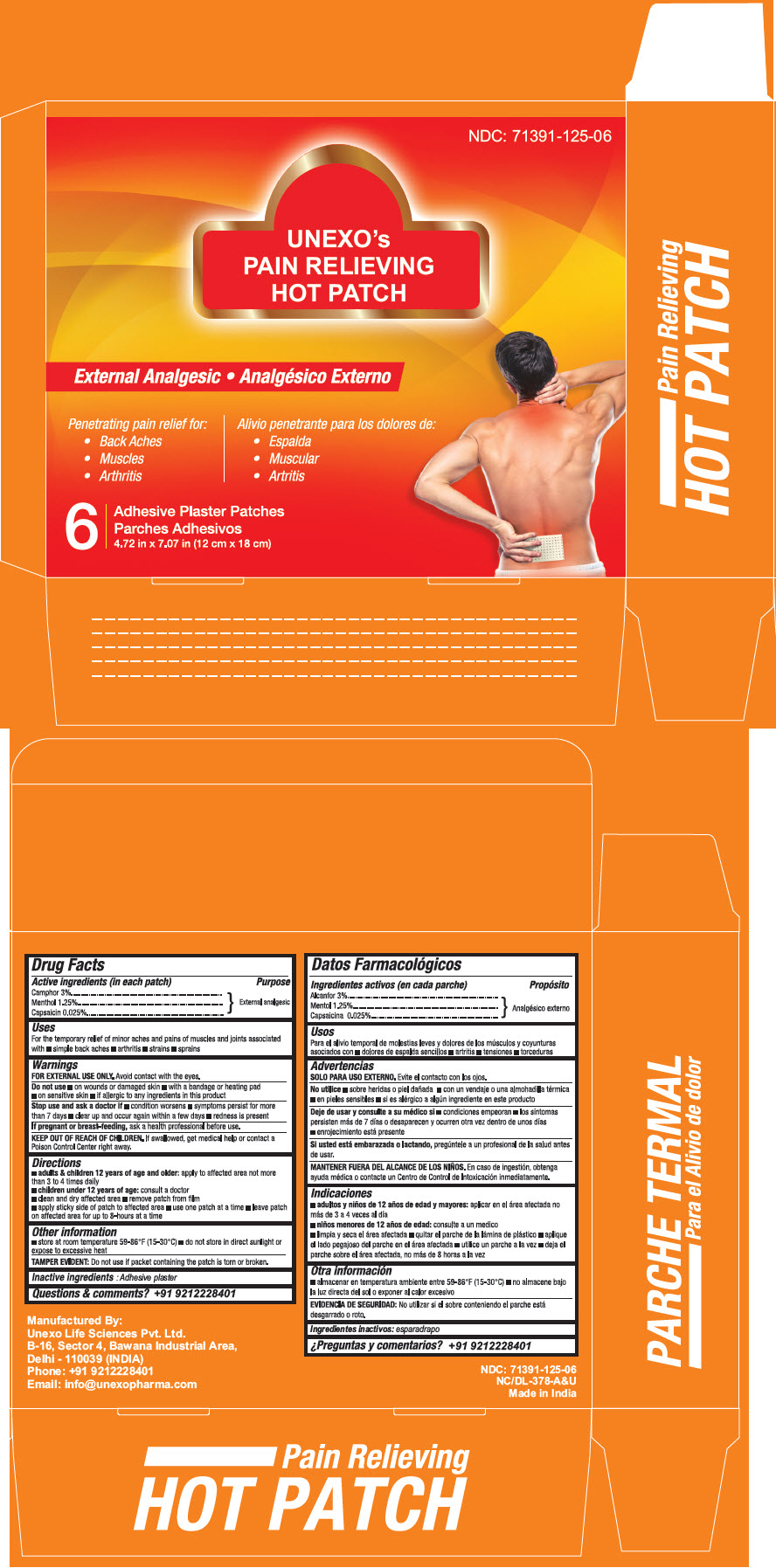 DRUG LABEL: CMC Pain Relieving
NDC: 71391-125 | Form: PATCH
Manufacturer: Unexo Life Sciences, Private Limited
Category: otc | Type: HUMAN OTC DRUG LABEL
Date: 20200526

ACTIVE INGREDIENTS: .ALPHA.,.ALPHA.-DIBROMO-D-CAMPHOR 129.6 mg/1 1; MENTHOL, UNSPECIFIED FORM 54 mg/1 1; CAPSAICIN 1.08 mg/1 1

CMC Pain Relieving Patch

Drug Facts

ACTIVE INGREDIENT

Active Ingredient
Camphor 3% | External Analgesic
Menthol 1.25% | External Analgesic
Capsaicin 0.025% | External Analgesic

Uses

For temporary relief of minor aches and pains of muscles and joints associated with:

- Simple backaches
- Arthritis
- Strains
- Sprains

Warnings

FOR EXTERNAL USE ONLY. Avoid contact with eyes.

Do not use

- On wounds or damaged skin
- With a bandage or heating pad
- On sensitive skin
- if allergic to any ingredient in this product

Stop use and ask a doctor if

- Condition worsens
- symptoms persist for more than 7 days
- clear up and occur again within a few days
- redness is present

PREGNANCY OR BREAST FEEDING

If pregnant or breast-feeding, ask a health professional before use.

KEEP OUT OF REACH OF CHILDREN. If swallowed, get medical help or contact a Poison Control Center right away.

Directions

- Adults and children 12 years of age and older: apply to the affected area not more than 3 to 4 times daily
- Children under 12 years of age consult a doctor
- clean and dry affected area
- remove patch from film
- apply sticky side of patch to affected area
- use one patch at a time
- leave patch on affected area for up to 8 hours at a time

Other Information

- Store at room temperature 59-86°F (15-30°C)
- Do not store in direct sunlight or expose to excessive heat

TAMPER EVIDENT: Do not use if packet containing the patch is torn or broken

Inactive Ingredients

Adhesive plaster

Questions

Call +91 9212228401

Manufactured By:
UNEXO LIFE SCIENCES PVT. LTD.
B-16. Sector 4, Bawana Industrial Area,
Delhi – 110039 (INDIA)

PRINCIPAL DISPLAY PANEL - 6 Pouch Box

NDC: 71391-125-06

UNEXO's
PAIN RELIEVING
HOT PATCH

External Analgesic

Penetrating pain relief for:

- Back Aches
- Muscles
- Arthritis

6
Adhesive Plaster Patches
4.72 in x 7.07 in (12 cm x 18 cm)